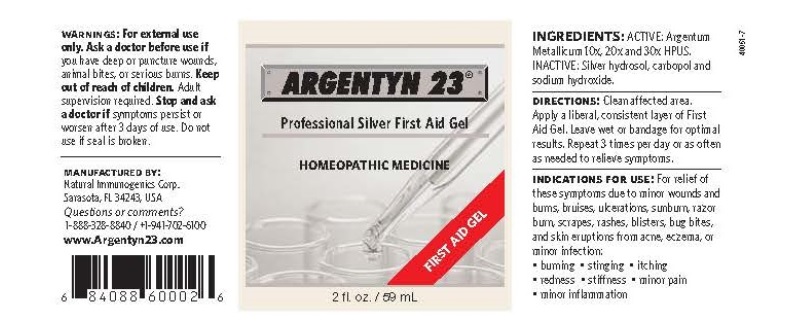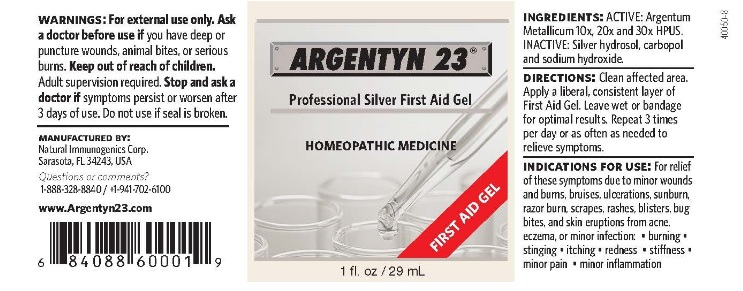 DRUG LABEL: Argentyn 23

NDC: 52166-001 | Form: GEL
Manufacturer: Natural Immunogenics Corp.dba SOVEREIGN NATURALS
Category: homeopathic | Type: HUMAN OTC DRUG LABEL
Date: 20251015

ACTIVE INGREDIENTS: SILVER 30 [hp_X]/1 mL
INACTIVE INGREDIENTS: CARBOMER HOMOPOLYMER TYPE B (ALLYL PENTAERYTHRITOL CROSSLINKED); SODIUM HYDROXIDE

HOMEOPATHIC DRUG

Ingredients: ACTIVE:

Argentum Mettalicum 10x, 20x and 30x HPUS

Inactive: Silver Hydrosol, carbopol

and Sodium hydroxide

PURPOSE

First Aid Gel

Homeopathic Medicine

Keep out of reach of children

Warnings. For external use only.

Ask a doctor before use of you have deep or puncture wounds,

animal bites or serious burns.

Adult supervision required.

DOSAGE AND ADMINISTRATION

Directions. Clean affected area. Apply a liberal,

consistent layer of First Aid Gel. Leave wet or bandage for optimal results. Repeat 3 times

per day or as often as needed to relieve symptoms

Indications for Use: For relief of these symptoms

due to minor wounds and burns, bruises, ulcerations,

sunburn, razor burn, scrapes, rashes, blisters, bug bites,

and skin eruptions form acne, eczema, or minor infection:

burning

stinging

itching

redness

stiffness

minor pain

minor inflammation